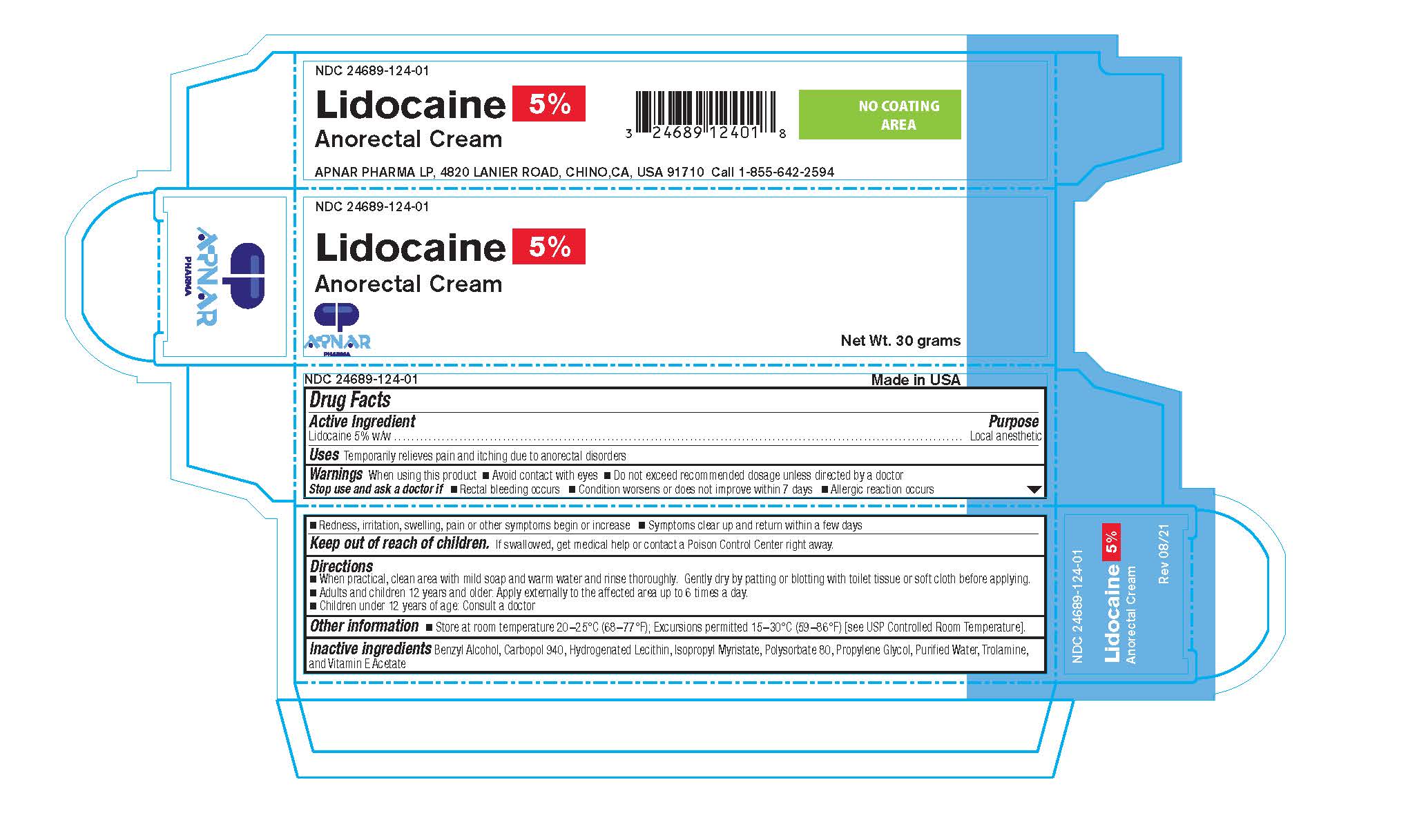 DRUG LABEL: Lidocaine 5%
NDC: 24689-124 | Form: CREAM
Manufacturer: Apnar Pharma LP
Category: otc | Type: HUMAN OTC DRUG LABEL
Date: 20231021

ACTIVE INGREDIENTS: LIDOCAINE 5 g/100 g
INACTIVE INGREDIENTS: POLYSORBATE 80; HYDROGENATED SOYBEAN LECITHIN; ISOPROPYL MYRISTATE; BENZYL ALCOHOL; CARBOMER 940; PROPYLENE GLYCOL; ALPHA-TOCOPHEROL ACETATE; WATER; TROLAMINE

Lidocaine 5% Anorectal Cream

ACTIVE INGREDIENT

Lidocaine 5% w/w

PURPOSE

Local Anesthetic

Uses Temporarily relieves pain and itching due to anorectal disorders

When using this product

- Avoid contact with eyes
- Do not exceed recommended dosage unless directed by a doctor

ASK DOCTOR

- Rectal bleeding occurs
- Condition worsens or does not improve within 7 days
- Allergic reaction occurs
- Redness, irritation, swelling, pain or other symptoms begin or increase
- Symptoms clear up and return within a few days

KEEP OUT OF REACH OF CHILDREN

If swallowed, get medical help or contact a Poison Control Center right away.

DIRECTIONS

- When practical, clean area with mild soap and warm water and rinse thoroughly. Gently dry by patting or blotting with toilet tissue or soft cloth before applying.
- Adults and children 12 years and older: Apply externally to the affected area up to 6 times a day.
- Children under 12 years of age: Consult a doctor

OTHER SAFETY INFORMATION

Store at room temperature 20-25°C (68-77°F); Excursions permitted 15-30°C (59-86°F) [see USP Controlled Room Temperature].

INACTIVE INGREDIENT

Benzyl Alcohol, Carbopol 940 (Carbomer 940), Hydrogenated Lecithin, Isopropyl Myristate, Polysorbate 80, Propylene Glycol, Purified Water, Trolamine, and Vitamin E Acetate (Alpha Tocophferol Acetate)

DOSAGE

50 miligrams/gram per application

USAGE

Adults and children 12 years and older: Apply externally to the affected area up to 6 times a day.
Children under 12 years of age: Consult a doctor

PACKAGE LABEL

NDC 24689-124-01

Lidocaine 5% Anorectal Cream

Apnar Pharma LP

Net.Wt 30 grams